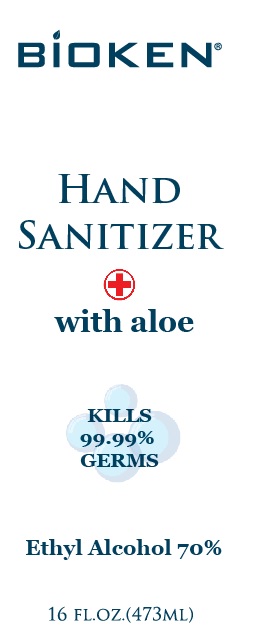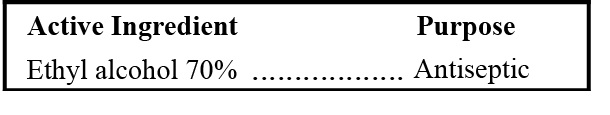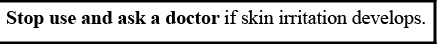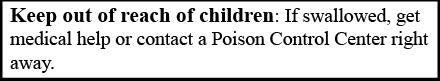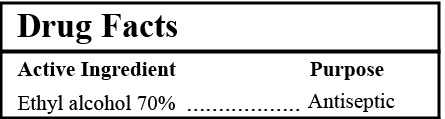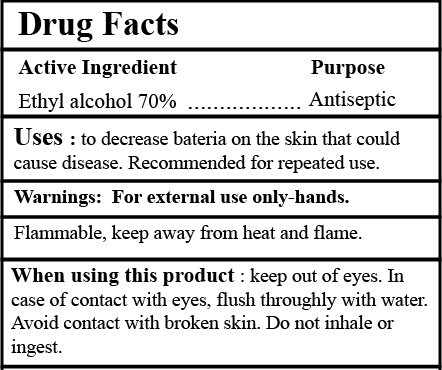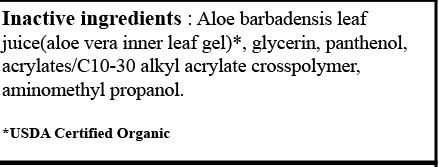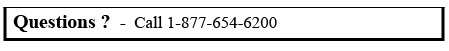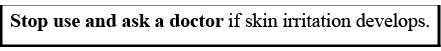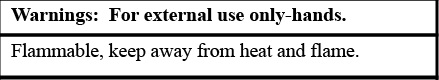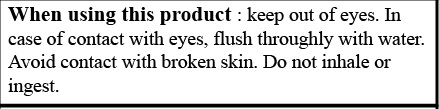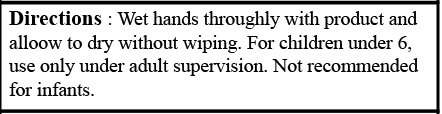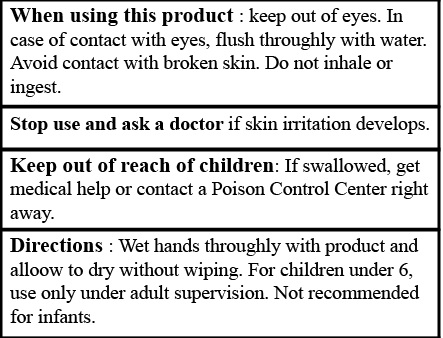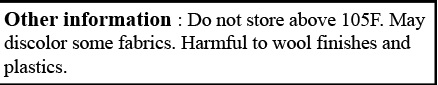 DRUG LABEL: 70% Bioken Hand Sanitizer with aloe
NDC: 71331-107 | Form: GEL
Manufacturer: Orange Lab
Category: otc | Type: HUMAN OTC DRUG LABEL
Date: 20220201

ACTIVE INGREDIENTS: ALCOHOL 70 mL/100 mL
INACTIVE INGREDIENTS: AMINOMETHYLPROPANOL 0.3 mL/100 mL; GLYCERIN 4 mL/100 mL; PANTHENOL 0.5 mL/100 mL; CARBOMER COPOLYMER TYPE A 0.3 mL/100 mL; ALOE VERA LEAF 25.1 mL/100 mL

Bioken Hand Sanitizer with Aloe 70% 16oz